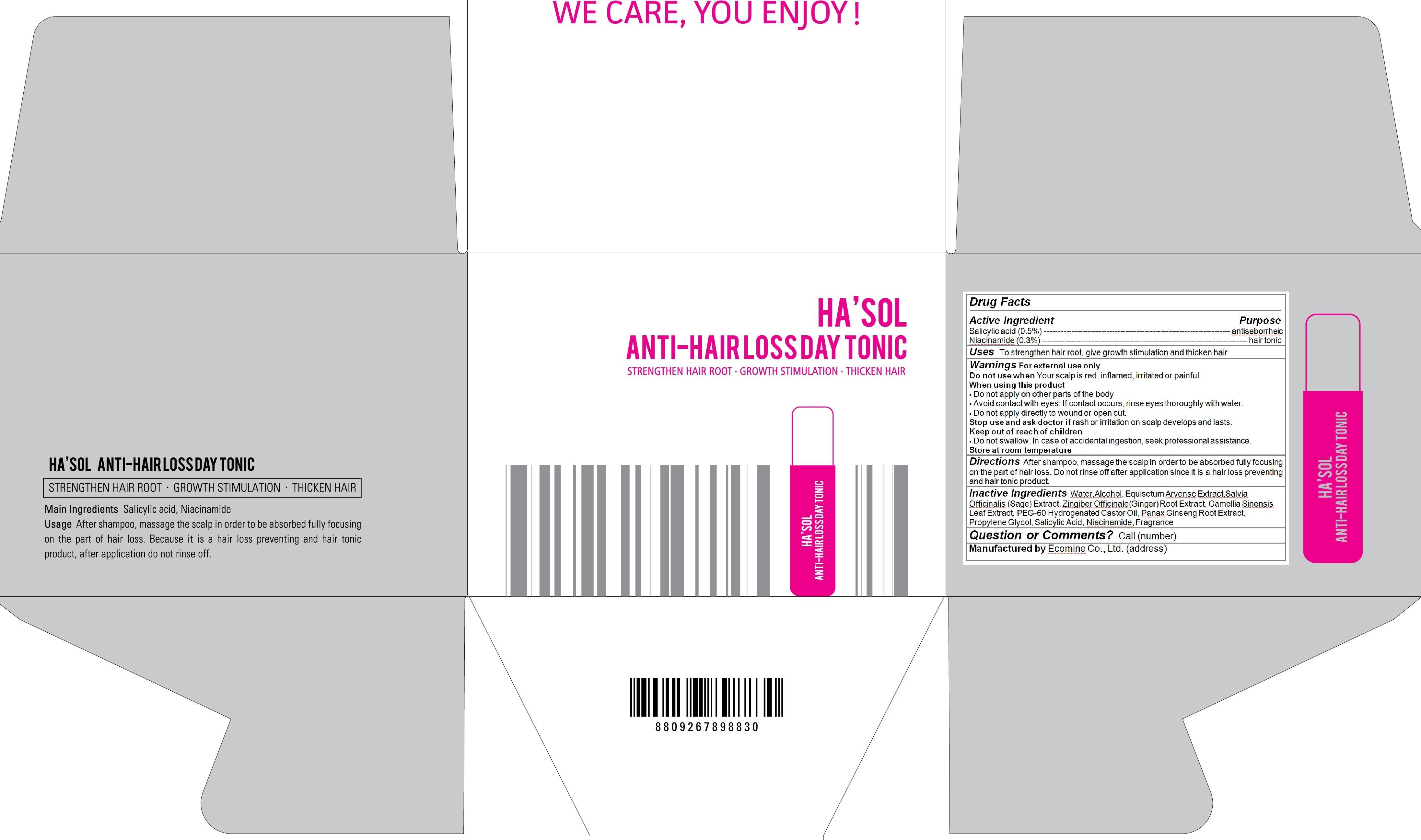 DRUG LABEL: Hasol Anti hair loss day tonic
NDC: 51270-117 | Form: LIQUID
Manufacturer: Ecomine Co., Ltd.
Category: otc | Type: HUMAN OTC DRUG LABEL
Date: 20131224

ACTIVE INGREDIENTS: Salicylic Acid 0.375 g/75 g; Niacinamide 0.225 g/75 g
INACTIVE INGREDIENTS: water; Alcohol; EQUISETUM ARVENSE WHOLE; SALVIA OFFICINALIS WHOLE; ZINGIBER OFFICINALE WHOLE; CAMELLIA SINENSIS WHOLE; PEG-60 HYDROGENATED CASTOR OIL; PANAX GINSENG ROOT OIL; Propylene Glycol

Hasol Anti hair loss day tonic